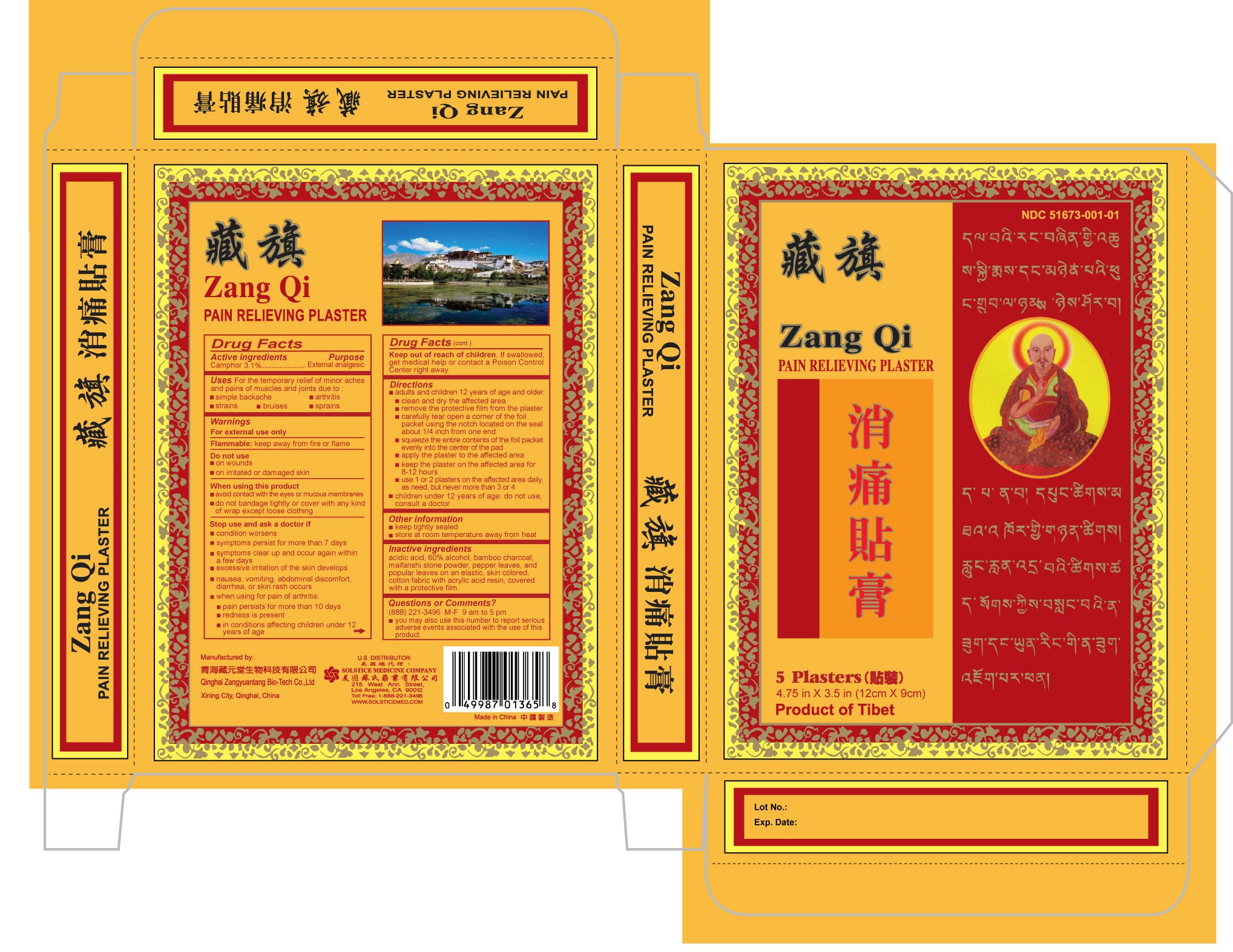 DRUG LABEL: ZANG QI
NDC: 51673-001 | Form: PLASTER
Manufacturer: QINGHAI ZANGYUANTANG BIO-TECH CO LTD
Category: otc | Type: HUMAN OTC DRUG LABEL
Date: 20100604

ACTIVE INGREDIENTS: CAMPHOR (NATURAL) 3.1 g/1 1

DRUG FACTS

Active ingredient

Camphor 3.1%

Purpose

Topical analgesic

Uses For the temporary relief of minor aches and pains of muscles and joint due to:

- simple backache
- arthritis
- strains
- bruises
- sprains

Do not use

- on wounds
- on irritated or damaged skin

When using this product

- avoid contact with the eyes and mucous membranes
- do not bandage tightly or cover with any kind of wrap except loose clothing

Stop use and ask a doctor if

- condition worsens
- symptoms persist for more than 7 days
- symptoms clear up and occur again within a few days
- excessive irritation of the skin develops
- nausea, vomiting, abdominal discomfort, diarrhea, or skin rash occurs
- when using for pain of arthritis:
-
  - if pain persists for more than 10 days
  - if redness is present
  - in conditions affecting children under 12 years of age

Keep out of reach of children. If swallowed, get medical help or contact a
Poison Control Center right away.

Directions

- adults and children 12 years of age and older:
-
  - clean and dry the affected area
  - remove the protective film from the plaster
  - carefully tear open a corner of the foil packet using the notch located on the seal about 1/4 inch from one end
  - squeeze the entire contents of the foil packet evenly into the center of the pad
  - apply the plaster to the affected area
  - keep the plaster on the affected area for 8-12 hours
  - use 1 or 2 plasters on the affected area daily, as need, but never more than 3 or 4

- children under 12 years of age: do not use, consult a doctor

Other information

- keep tightly sealed, protected from light
- store at room temperature away from heat

Inactive ingredients acidic acid, 60% alcohol, bamboo charcoal,
maifanshi stone powder, pepper leaves, and poplar leaves on an elastic, skin
colored, cotton fabric with acrylic acid resin, covered with a protective film.

Questions or Comments? (888) 221-3496 M-F 9 am to 5 pm

- you may also use this number to report serious adverse events associated with the use of this product

PACKAGE LABEL

ZANG QI PAIN RELIEVING PLASTER NDC 51673-001-01 5 PLASTERS EACH PLASTER 4.75 IN X 3.5 IN (12 CM X 9 CM)